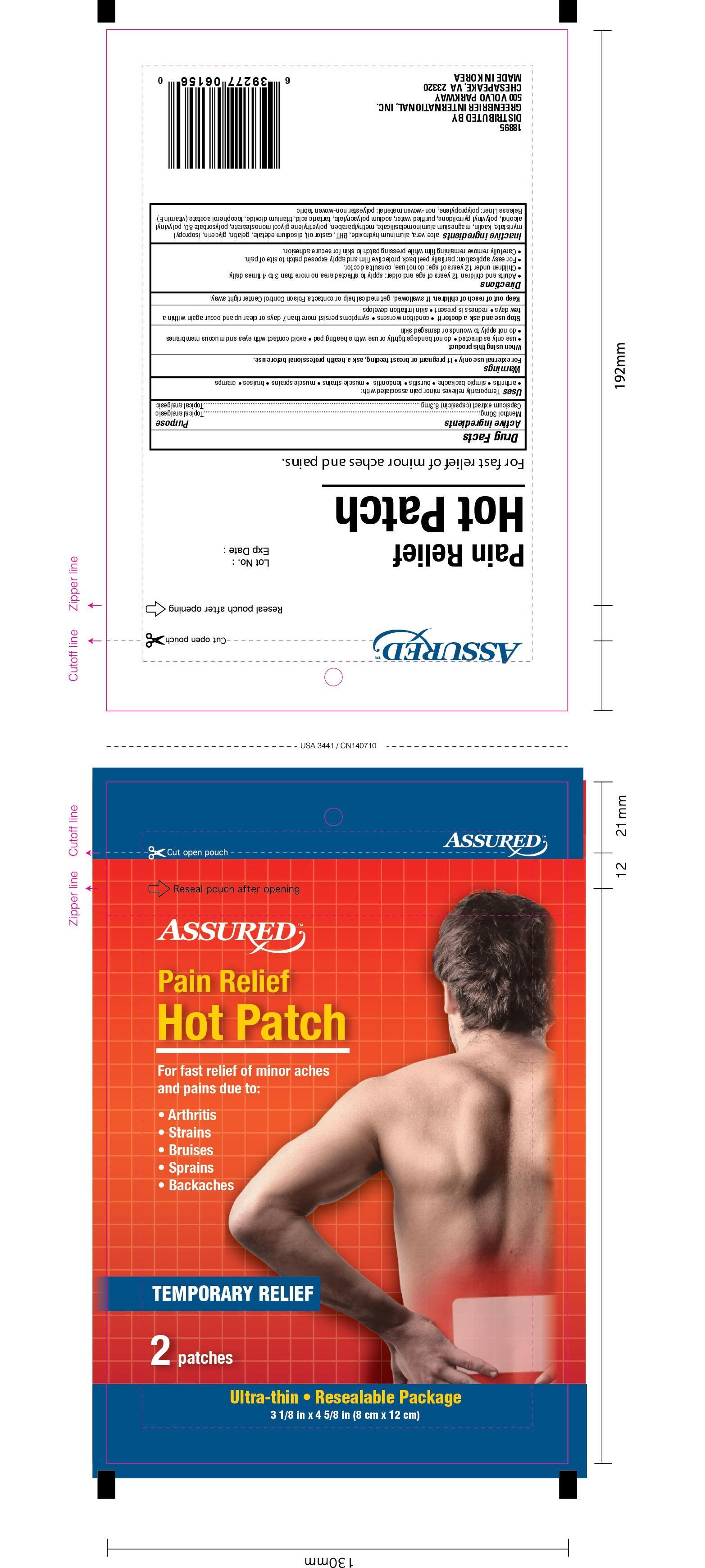 DRUG LABEL: Assured Pain Relief Hot Menthol
NDC: 33992-6156 | Form: PATCH
Manufacturer: Greenbrier International, Inc
Category: otc | Type: HUMAN OTC DRUG LABEL
Date: 20191205

ACTIVE INGREDIENTS: MENTHOL 30 mg/100 mg; CAPSAICIN 8.3 mg/100 mg
INACTIVE INGREDIENTS: ALOE VERA LEAF; ALUMINUM HYDROXIDE; CASTOR OIL; EDETATE DISODIUM; GELATIN; GLYCERIN; ISOPROPYL MYRISTATE; KAOLIN; MAGNESIUM ALUMINUM SILICATE; METHYLPARABEN; POLYETHYLENE GLYCOL 1000; POLYSORBATE 80; POLYVINYL ALCOHOL; WATER; SODIUM POLYACRYLATE (8000 MW); TARTARIC ACID; TITANIUM DIOXIDE; .ALPHA.-TOCOPHEROL ACETATE

Assured Pain Relief Hot Patches, 2ct 6156, 2019

Active Ingredient Purpose

Menthol 30mg--------------------------------------------------------- Topical analgestic

Capsicum extract (capsaicin) 8.3mg--------------------------------- Topical analgestic

PURPOSE

Uses Temporarily relieves minor pain associated with:

- arthritis
- simple backche
- bursitis
- tendonitis
- muscle strains
- music sprains
- bruises
- cramps

WARNINGS

For external use only

- If pregnant or breast feeding, ask a health professional before use.

When using this product

- use as only directed
- do not bandage tightly or use with a heating pad
- avoid contact with eyes and mucous membranes
- do not apply to wounds or damaged skin

Stop use and ask a doctor if

- condition worsens
- symptoms persist more than 7 days or clear up and occur again within a few days
- redness is present
- skin irritation develops
- do not apply to wounds or damanged skin

Keep out of reach of chidren.

If swallowed, get medical help or contact a Poison Control Center right away.

Directions

- Adults and children 12 years of age and older: apply to affected area no more than 3 to 4 times daily.
- Children under 12 years of age: do not use, consult a doctor.
- For easy application: partially peel back protective film and apply exposed film and apply exposed patch to site of pain.
- Carefully remove remaining film while pressing patch to skin for secure adhesion.

Inactive ingredients

aloe vera, aluminum hydroxide, BHT, castor oil, disodium edetate, gelatin, glycerin, isopropyl myristate, kaolin, magnesium aluminometasilicate, methylparaben, polyethylene glycol monostearate, polysorbate 80, polyvinyl alcohol, polyvinyl pyrrolidone, purified water, sodium polyacrylate, tartaric acid, tatanium dioxide, tocopherol acetate

Release liner: polypropylene, non-woven material: polyester non-woven fabric

DOSAGE AND ADMINISTRATION

DISTRIBUTED BY

GREENBRIER INTERNATIONAL, INC.

500 VOLVO PARKWAY

CHESAPEAKE, VA 23320

MADE IN KOREA